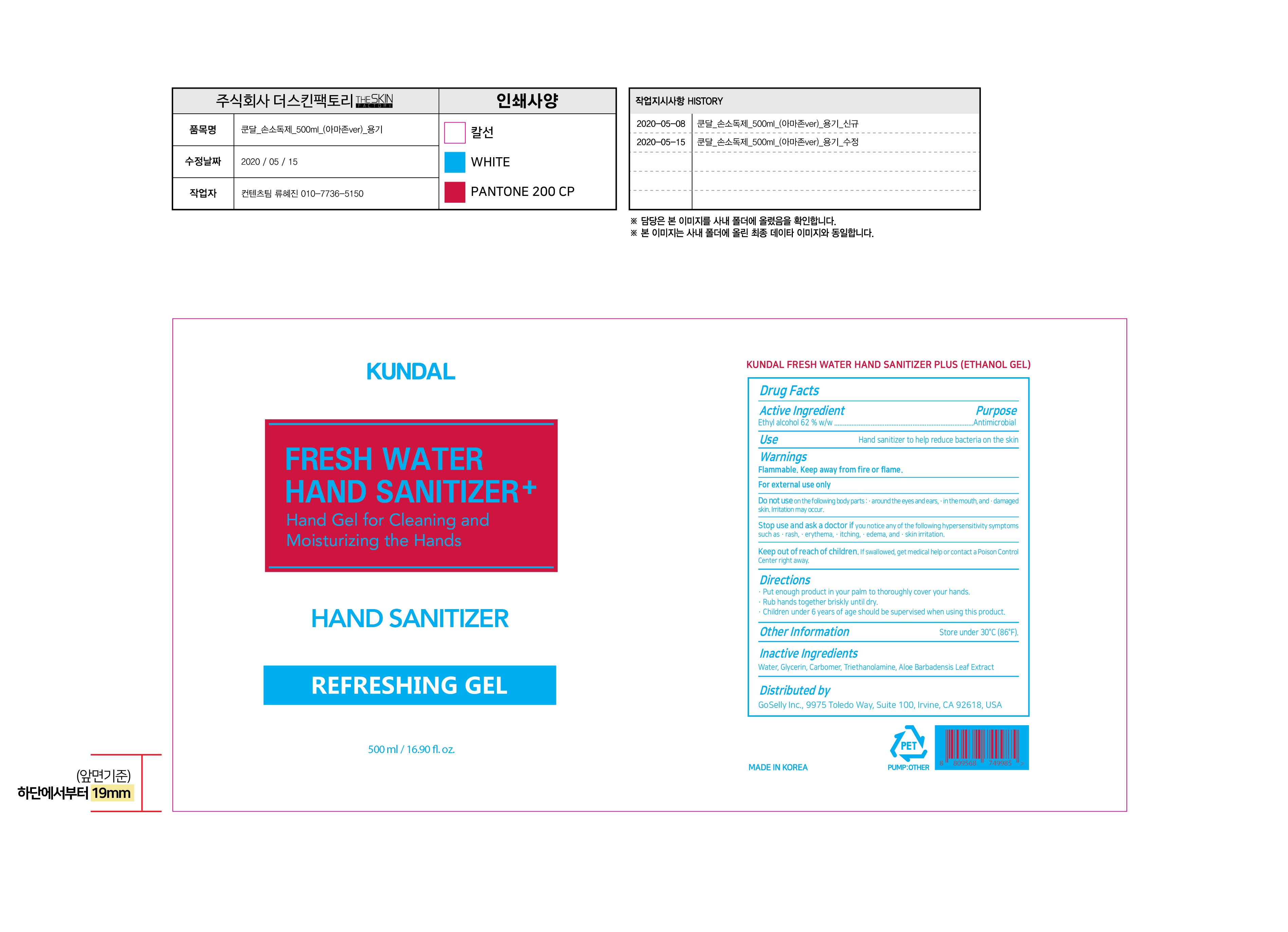 DRUG LABEL: Kundal Fresh Water Hand Sanitizer Plus
NDC: 73330-0040 | Form: GEL
Manufacturer: COSNINE, Inc.
Category: otc | Type: HUMAN OTC DRUG LABEL
Date: 20200515

ACTIVE INGREDIENTS: ALCOHOL 310 mL/500 mL
INACTIVE INGREDIENTS: CARBOMER HOMOPOLYMER, UNSPECIFIED TYPE; TROLAMINE; WATER; GLYCERIN; ALOE

Drug Facts

ACTIVE INGREDIENT

Alcohol

INACTIVE INGREDIENT

Water, Glycerin, Carbomer, Triethanolamine, Aloe Barbadensis Leaf Extract

PURPOSE

Antimicrobial

KEEP OUT OF REACH OF THE CHILDREN

INDICATIONS AND USAGE

Store under 30°C (86°F)

WARNINGS

For external use only.

Flammable, keep away from fire or flame.

When using this product keep out of eyes. If contact with eyes occurs, rinse promptly and thoroughly with water.

Stop use and ask a doctor if significant irritation or sensitization develops.

Keep out of reach of children. If swallowed, get medical help or contact a Poison Control Center right away.

DOSAGE AND ADMINISTRATION

- Put enough product in your palm to thoroughly cover your hands
- Rub hands together briskly until dry
- Children under 6 years of age should be supervised when using this product